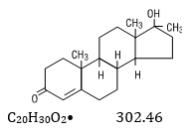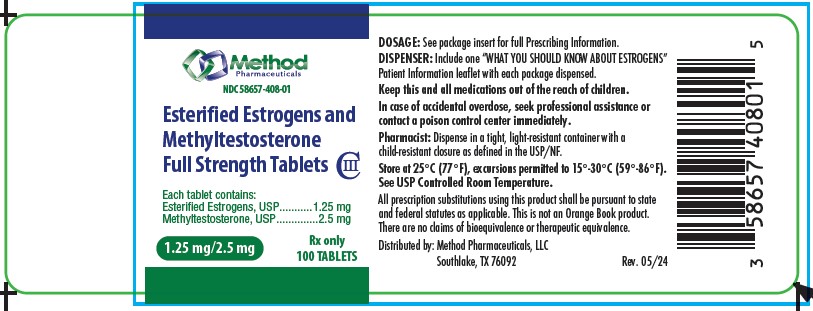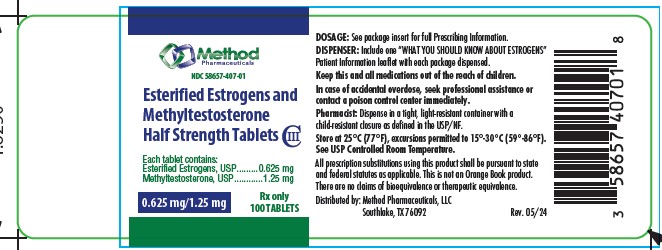 DRUG LABEL: ESTERIFIED ESTROGENS AND METHYLTESTOSTERONE
NDC: 58657-407 | Form: TABLET
Manufacturer: Method Pharmaceuticals, LLC
Category: prescription | Type: HUMAN PRESCRIPTION DRUG LABEL
Date: 20251021
DEA Schedule: CIII

ACTIVE INGREDIENTS: ESTROGENS, ESTERIFIED 0.625 mg/1 1; METHYLTESTOSTERONE 1.25 mg/1 1
INACTIVE INGREDIENTS: MICROCRYSTALLINE CELLULOSE; LACTOSE MONOHYDRATE; MAGNESIUM STEARATE; WATER; TITANIUM DIOXIDE; D&C YELLOW NO. 10; FD&C BLUE NO. 1

Physician Labeling

ESTERIFIED ESTROGENS AND METHYLTESTOSTERONE Tablets

WARNINGS

1. ESTROGENS HAVE BEEN REPORTED TO INCREASE THE RISK OF ENDOMETRIAL CARCINOMA

Three independent case control studies have reported an increased risk of endometrial cancer in postmenopausal women exposed to exogenous estrogens for prolonged periods.^1-3 This risk was independent of the other known risk factors for endometrial cancer. These studies are further supported by the finding that incidence rates of endometrial cancer have increased sharply since 1969 in eight different areas of the United States with population-based cancer reporting systems, an increase which may be related to the rapidly expanding use of estrogens during the last decade.^4

The three case control studies reported that the risk of endometrial cancer in estrogen users was about 4.5 to 13.9 times greater than in nonusers. The risk appears to depend on both duration of treatment^1 and on estrogen dose.^3In view of these findings, when estrogens are used for the treatment of menopausal symptoms, the lowest dose that will control symptoms should be utilized and medication should be discontinued as soon as possible. When prolonged treatment is medically indicated, the patient should be reassessed on at least a semiannual basis to determine the need for continued therapy. Although the evidence must be considered preliminary, one study suggests that cyclic administration of low doses of estrogen may carry less risk than continuous administration,^3 it therefore appears prudent to utilize such a regimen.

Close clinical surveillance of all women taking estrogens is important. In all cases of undiagnosed persistent or recurring abnormal vaginal bleeding, adequate diagnostic measures should be undertaken to rule out malignancy.

There is no evidence at present that "natural" estrogens are more or less hazardous than "synthetic" estrogens at equiestrogenic doses.

2. ESTROGENS SHOULD NOT BE USED DURING PREGNANCY

The use of female sex hormones, both estrogens and progestogens, during early pregnancy may seriously damage the offspring. It has been shown that females exposed in utero to diethylstilbestrol, a non-steroidal estrogen, have an increased risk of developing in later life a form of vaginal or cervical cancer that is ordinarily extremely rare.^5,6 This risk has been estimated as not greater than 4 per 1000 exposures.^7 Furthermore, a high percentage of such exposed women (from 30 to 90 percent) have been found to have vaginal adenosis,^8-12 epithelial changes of the vagina and cervix. Although these changes are histologically benign, it is not known whether they are precursors of malignancy. Although similar data are not available with the use of other estrogens, it cannot be presumed they would not induce similar changes.

Several reports suggest an association between intrauterine exposure to female sex hormones and congenital anomalies, including congenital heart defects and limb reduction defects.^13-16 One case control study^16 estimated a 4.7 fold increased risk of limb reduction defects in infants exposed in utero to sex hormones (oral contraceptives, hormone withdrawal tests for pregnancy, or attempted treatment for threatened abortion). Some of these exposures were very short and involved only a few days of treatment. The data suggest that the risk of limb reduction defects in exposed fetuses is somewhat less than 1 per 1000.

In the past, female sex hormones have been used during pregnancy in an attempt to treat threatened or habitual abortion. There is considerable evidence that estrogens are ineffective for these indications, and there is no evidence from well controlled studies that progesterones are effective for these uses.

IF ESTERIFIED ESTROGENS AND METHYLTESTOSTERONE FULL STRENGTH or ESTERIFIED ESTROGENS AND METHYLTESTOSTERONE HALF STRENGTH is used during pregnancy, or if the patient becomes pregnant while taking this drug, she should be apprised of the potential risks to the fetus, and the advisability of pregnancy continuation.

DESCRIPTION

ESTERIFIED ESTROGENS AND METHYLTESTOSTERONE FULL STRENGTH: Each light pink, capsule-shaped, film-coated oral tablet contains: 0.65 mg of Esterified Estrogens, USP and 1.25 mg of Methyltestosterone, USP.

ESTERIFIED ESTROGENS AND METHYLTESTOSTERONE HALF STRENGTH: Each light yellow, capsule-shaped, film-coated oral tablet contains: 1.25 mg of Esterified Estrogens, USP and 2.5 mg of Methyltestosterone, USP.

Esterified Estrogens

Esterified Estrogens, USP is a mixture of the sodium salts of the sulfate esters of the estrogenic substances, principally estrone, that are of the type excreted by pregnant mares. Esterified Estrogens contain not less than 75.0 percent and not more than 85.0 percent of sodium estrone sulfate, and not less than 6.0 percent and not more than 15.0 percent of sodium equilin sulfate, in such proportion that the total of these two components is not less than 90.0 percent.

Category: Estrogens

Methyltestosterone

Methyltestosterone is an androgen. Androgens are derivatives of cyclopentano-perhydrophenanthrene. Endogenous androgens are C-19 steroids with a side chain at C-17, and with two angular methyl groups. Testosterone is the primary endogenous androgen. Fluoxymesterone and methyltestosterone are synthetic derivatives of testosterone.

Methyltestosterone is a white to light yellow crystalline substance that is virtually insoluble in water but soluble in organic solvents. It is stable in air but decomposes in light.

Methyltestosterone structural formula:

Androst-4-en-3-one, 17-hydroxy-17-methyl-, (17B)-. Category: Androgen.

ESTERIFIED ESTROGENS AND METHYLTESTOSTERONE FULL STRENGTH TABLETS and ESTERIFIED ESTROGENS AND METHYLTESTOSTERONE HALF STRENGTH TABLETS contain the following inactive ingredients: lactose, magnesium stearate, microcrystalline cellulose, titanium dioxide, and other minor ingredients.

ESTERIFIED ESTROGENS AND METHYLTESTOSTERONE FULL STRENGTH TABLETS also contain: FD&C Blue No. 1 and D&C Yellow No. 10 and PEG.

ESTERIFIED ESTROGENS AND METHYLTESTOSTERONE HALF STRENGTH TABLETS also contain: D&C Yellow No. 10, FD&C Blue No. 1.

CLINICAL PHARMACOLOGY

Estrogens

Estrogens are important in the development and maintenance of the female reproductive system and secondary sex characteristics. They promote growth and development of the vagina, uterus, and fallopian tubes, and enlargement of the breasts. Indirectly, they contribute to the shaping of the skeleton, maintenance of tone and elasticity of urogenital structures, changes in the epiphyses of the long bones that allow for the pubertal growth spurt and its termination, growth of axillary and pubic hair, and pigmentation of the nipples and genitals. Decline of estrogenic activity at the end of the menstrual cycle can bring on menstruation, although the cessation of progesterone secretion is the most important factor in the mature ovulatory cycle. However, in the preovulatory or nonovulatory cycle, estrogen is the primary determinant in the onset of menstruation. Estrogens also affect the release of pituitary gonadotropins. The pharmacologic effects of esterified estrogens are similar to those of endogenous estrogens. They are soluble in water and are well absorbed from the gastrointestinal tract.

In responsive tissues (female genital organs, breasts, hypothalamus, pituitary) estrogens enter the cell and are transported into the nucleus. As a result of estrogen action, specific RNA and protein synthesis occurs.

Estrogen Pharmacokinetics

Metabolism and inactivation occur primarily in the liver. Some estrogens are excreted into the bile; however they are reabsorbed from the intestine and returned to the liver through the portal venous system. Water soluble esterified estrogens are strongly acidic and are ionized in body fluids, which favor excretion through the kidneys since tubular reabsorption is minimal.

Androgens

Endogenous androgens are responsible for the normal growth and development of the male sex organs and for maintenance of secondary sex characteristics. These effects include the growth and maturation of prostate, seminal vesicles, penis, and scrotum; the development of male hair distribution, such as beard, pubic, chest and axillary hair, laryngeal enlargement, vocal cord thickening, alterations in body musculature, and fat distribution. Drugs in this class also cause retention of nitrogen, sodium, potassium, phosphorus, and decreased urinary excretion of calcium. Androgens have been reported to increase protein anabolism and decrease protein catabolism. Nitrogen balance is improved only when there is sufficient intake of calories and protein. Androgens are responsible for the growth spurt of adolescence and for the eventual termination of linear growth centers. In children, exogenous androgens accelerate linear growth rates, but may cause a disproportionate advancement in bone maturation. Use over long periods may result in fusion of the epiphyseal growth centers and termination of growth process. Androgens have been reported to stimulate the production of red blood cells by enhancing the production of erythropoietic stimulating factor.

Androgen Pharmacokinetics

Testosterone given orally is metabolized by the gut and 44 percent is cleared by the liver in the first pass. Oral doses as high as 400 mg per day are needed to achieve clinically effective blood levels for full replacement therapy. The synthetic androgens (methyltestosterone and fluoxymesterone) are less extensively metabolized by the liver and have longer half-lives. They are more suitable than testosterone for oral administration.

Testosterone in plasma is 98 percent bound to a specific testosterone estradiol binding globulin, and about 2 percent is free. Generally, the amount of this sex-hormone binding globulin in the plasma will determine the distribution of testosterone between free and bound forms, and the free testosterone concentration will determine its half-life.

About 90 percent of a dose of testosterone is excreted in the urine as glucuronic and sulfuric acid conjugates of testosterone and its metabolites; about 6 percent of a dose is excreted in the feces, mostly in the unconjugated form. Inactivation of testosterone occurs primarily in the liver. Testosterone is metabolized to various 17-keto steroids through two different pathways. There are considerable variations of the half-life of testosterone as reported in the literature, ranging from 10 to 100 minutes.

In many tissues the activity of testosterone appears to depend on reduction to dihydrotestosterone, which binds to cytosol receptor proteins. The steroid-receptor complex is transported to the nucleus where it initiates transcription events and cellular changes related to androgen action.

INDICATIONS AND USAGE

ESTERIFIED ESTROGENS AND METHYLTESTOSTERONE FULL STRENGTH and ESTERIFIED ESTROGENS AND METHYLTESTOSTERONE HALF STRENGTH are indicated in the treatment of: Moderate to severe vasomotorsymptoms associated with the menopause in those patients not improved by estrogens alone. (There is no evidence that estrogens are effective for nervous symptoms or depression without associated vasomotor symptoms, and they should not be used to treat such conditions.)

ESTERIFIED ESTROGENS AND METHYLTESTOSTERONE FULL STRENGTH and ESTERIFIED ESTROGENS AND METHYLTESTOSTERONE HALF STRENGTH HAVE NOT BEEN SHOWN TO BE EFFECTIVE FOR ANY PURPOSE DURING PREGNANCY AND ITS USE MAY CAUSE SEVERE HARM TO THE FETUS (SEE BOXED WARNING).

CONTRAINDICATIONS

Estrogens should not be used in women with any of the following conditions:

1. Known or suspected cancer of the breast except in appropriately selected patients being treated for metastatic disease.

2. Known or suspected estrogen-dependent neoplasia.

3. Known or suspected pregnancy (See Boxed Warning).

4. Undiagnosed abnormal genital bleeding.

5. Active thrombophlebitis or thromboembolic disorders.

6. A past history of thrombophlebitis, thrombosis, or thromboembolic disorders associated with previous estrogen use (except when in treatment of breast malignancy).

Methyltestosterone should not be used in:

1. The presence of severe liver damage.

2. Pregnancy and in breast-feeding mothers because of the possibility of masculinization of the female fetus or breast-fed infant.

WARNINGS

Associated with Estrogens

1. Induction of malignant neoplasms. Long term continuous administration of natural and synthetic estrogens in certain animal species increases this frequency of carcinomas of the breast, cervix, vagina, and liver. There is now evidence that estrogens increase the risk of carcinoma of the endometrium in humans (See Boxed Warning).

At the present time there is no satisfactory evidence that estrogens given to postmenopausal women increase the risk of cancer of the breast,^18although a recent long-term follow-up of a single physician's practice has raised this possibility.18aBecause of the animal data, there is a need for caution in prescribing estrogens for women with a strong family history of breast cancer or who have breast nodules, fibrocystic disease, or abnormal mammograms.

2. Gallbladder disease. A recent study has reported a 2 to 3-fold increase in the risk of surgically confirmed gallbladder disease in women receiving postmenopausal estrogens,^18 similar to the 2-fold increase previously noted in users of oral contraceptives.19-24a In the case of oral contraceptives the increased risk appeared after two years of use.^24

3. Effects similar to those caused by estrogen-progesterone oral contraceptives. There are several serious adverse effects of oral contraceptives, most of which have not, up to now, been documented as consequences of postmenopausal estrogen therapy. This may reflect the comparatively low doses of estrogen used in postmenopausal women. It would be expected that the larger doses of estrogen used to treat prostatic or breast cancer or postpartum breast engorgement are more likely to result in these adverse effects, and, in fact, it has been shown that there is an increased risk of thrombosis in men receiving estrogens for prostatic cancer and women for postpartum breast engorgement.^20-23

a. Thromboembolic disease. It is now well established that users of oral contraceptives have an increased risk of various thromboembolic and thrombotic vascular diseases, such as thrombophlebitis, pulmonary embolism, stroke, and myocardial infarction.^24-31 Cases of retinal thrombosis, mesenteric thrombosis, and optic neuritis have been reported in oral contraceptive users. There is evidence that the risk of several of these adverse reactions is related to the dose of the drug.^32-33 An increased risk of postsurgery thromboembolic complications has also been reported in users of oral contraceptives.^34-35 If feasible, estrogen should be discontinued at least 4 weeks before surgery of the type associated with an increased risk of thromboembolism, or during periods of prolonged immobilization.

While an increased rate of thromboembolic and thrombotic disease in postmenopausal users of estrogens has not been found,^18-36 this does not rule out the possibility that such an increase may be present or that subgroups of women who have underlying risk factors or who are receiving relatively large doses of estrogens may have increased risk. Therefore estrogens should not be used in persons with active thrombophlebitis or thromboembolic disorders, and they should not be used (except in treatment of malignancy) in persons with a history of such disorders in association with estrogen use. They should be used with caution in patients with cerebral vascular or coronary artery disease and only for those in whom estrogens are clearly needed.

Large doses of estrogen (5 mg esterified estrogens per day), comparable to those used to treat cancer of the prostate and breast, have been shown in a large prospective clinical trial in men^37 to increase the risk of nonfatal myocardial infarction, pulmonary embolism and thrombophlebitis. When estrogen doses of this size are used, any of the thromboembolic and thrombotic adverse effects associated with oral contraceptive use should be considered a clear risk.

b. Hepatic adenoma. Benign hepatic adenomas appear to be associated with the use of oral contraceptives.^38-40 Although benign and rare, these may rupture and may cause death through intra-abdominal hemorrhage. Such lesions have not yet been reported in association with other estrogen or progestogen preparations but should be considered in estrogen users having abdominal pain and tenderness, abdominal mass, or hypovolemic shock. Hepatocellular carcinoma has also been reported in women taking estrogen-containing oral contraceptives.^39 The relationship of this malignancy to these drugs is not known at this time.

c. Elevated blood pressure. Increased blood pressure is not uncommon in women using oral contraceptives. There is now a report that this may occur with use of estrogens in the menopause^41and blood pressure should be monitored with estrogen use, especially if high doses are used.

d. Glucose tolerance. A worsening of glucose tolerance has been observed in a significant percentage of patients of estrogen-containing oral contraceptives. For this reason, diabetic patients should be carefully observed while receiving estrogens.

4. Hypercalcemia. Administration of estrogens may lead to severe hypercalcemia in patients with breast cancer and bone metastases. If this occurs, the drug should be stopped and appropriate measures taken to reduce the serum calcium level.

Associated with Methyltestosterone

In patients with breast cancer, androgen therapy may cause hypercalcemia by stimulating osteolysis. In this case the drug should be discontinued.

Prolonged use of high doses of androgens has been associated with the development of peliosis hepatis and hepatic neoplasms including hepatocellular carcinoma. (See PRECAUTIONS – Carcinogenesis).

Peliosis hepatis can be a life-threatening or fatal complication.

Cholestatic hepatitis and jaundice occur with 17-alpha-alkyl androgens at a relatively low dose. If cholestatic hepatitis with jaundice appears or if liver function tests become abnormal, the androgen should be discontinued and the etiology should be determined. Drug-induced jaundice is reversible when the medication is discontinued.

Edema with or without heart failure may be a serious complication in patients with preexisting cardiac, renal, or hepatic disease. In addition to discontinuation of the drug, diuretic therapy may be required.

PRECAUTIONS

Associated with Estrogens

A. General Precautions

1. A complete medical and family history should be taken prior to the initiation of any estrogen therapy. The pretreatment and periodic physical examinations should include special reference to blood pressure, breasts, abdomen, and pelvic organs, and should include a Papanicolaou smear. As a general rule, estrogen should not be prescribed for longer than one year without another physical examination being performed.

2. Fluid retention– Because estrogens may cause some degree of fluid retention, conditions which might be influenced by this factor such as asthma, epilepsy, migraine, and cardiac or renal dysfunction, require careful observation.

3. Certain patients may develop undesirable manifestations of excessive estrogenic stimulation, such as abnormal or excessive uterine bleeding, mastodynia, etc.

4. Oral contraceptives appear to be associated with an increased incidence of mental depression.24 Although it is not clear whether this is due to the estrogenic or progestogenic component of the contraceptive, patients with a history of depression should be carefully observed.

5. Preexisting uterine leiomyomata may increase in size during estrogen use.

6. The pathologist should be advised of estrogen therapy when relevant specimens are submitted.

7. Patients with a past history of jaundice during pregnancy have an increased risk of recurrence of jaundice while receiving estrogen-containing oral contraceptive therapy. If jaundice develops in any patient receiving estrogen, the medication should be discontinued while the cause is investigated.

8. Estrogens may be poorly metabolized in patients with impaired liver function and they should be administered with caution in such patients.

9. Because estrogens influence the metabolism of calcium and phosphorus, they should be used with caution in patients with metabolic bone diseases that are associated with hypercalcemia or in patients with renal insufficiency.

10. Because of the effects of estrogens on epiphyseal closure, they should be used judiciously in young patients in whom bone growth is not complete.

11. Certain endocrine and liver function tests may be affected by estrogen-containing oral contraceptives. The following similar changes may be expected with larger doses of estrogen:
a. Increased sulfobromophthalein retention.
b. Increased prothrombin and factors VII, VIII, IX and X; decreased antithrombin 3: increased norepinephrine induced platelet aggregability.
c. Increased thyroid binding globulin (TBG) leading to increased circulating total thyroid hormone, as measured by PBI, T4 by column, or T4 by radioimmunoassay. Free T3 resin uptakes is decreased, reflecting the elevated TBG; free T4 concentration is unaltered.
d. Impaired glucose tolerance.
e. Decreased pregnanediol excretion.
f. Reduced response to metyrapone test.
g. Reduced serum folate concentration.
h. Increased serum triglyceride and phospholipid concentration.

B. Information for the Patient

See text of Patient Package Insert which appears after the REFERENCES.

C. Pregnancy Category X

See CONTRAINDICATIONS and Boxed WARNING.

D. Nursing Mothers

As a general principle, the administration of any drug to nursing mothers should be done only when clearly necessary since many drugs are excreted in human milk.

Associated with Methyltestosterone

A. General Precautions

1. Women should be observed for signs of virilization (deepening of the voice, hirsutism, acne, clitoromegaly, and menstrual irregularities). Discontinuation of drug therapy at the time of evidence of mild virilism is necessary to prevent irreversible virilization. Such virilization is usual following androgen use at high doses.

2. Prolonged dosage of androgen may result in sodium and fluid retention. This may present a problem, especially in patients with compromised cardiac reserve or renal disease.

3. Hypersensitivity may occur rarely.

4. PBI may be decreased in patients taking androgens.

5. Hypercalcemia may occur. If this does occur, the drug should be discontinued.

B. Information for the Patient

The physician should instruct patients to report any of the following side effects of androgens:

Women:Hoarseness, acne, changes in menstrual periods, or more hair on the face.

All Patients:Any nausea, vomiting, changes in skin color of ankle swelling.

C. Laboratory Tests

1. Women with disseminated breast carcinoma should have frequent determination of urine and serum calcium levels during the course of androgen therapy (see WARNINGS).

2. Because of the hepatotoxicity associated with the use of 17-alpha-alkylated androgens, liver function tests should be obtained periodically.

3. Hemoglobin and hematocrit should be checked periodically for polycythemia in patients who are receiving high doses of androgens

.

D. Drug Interactions

1. AnticoagulantsC-17 substituted derivatives of testosterone, such as methandrostenolone, have been reported to decrease the anticoagulant requirements of patients receiving oral anticoagulants. Patients receiving oral anticoagulant therapy require close monitoring, especially when androgens are started or stopped.

2. Oxyphenbutazone. Concurrent administration of oxyphenbutazone and androgens may result in elevated serum levels of oxyphenbutazone.

3. Insulin. In diabetic patients the metabolic effects of androgens may decrease blood glucose and insulin requirements.

E. Drug/Laboratory Test Interferences

Androgens may decrease levels of thyroxine-binding globulin, resulting in decreased T4serum levels and increased resin uptake of T3and T4. Free thyroid hormone levels remain unchanged, however, and there is no clinical evidence of thyroid dysfunction.

F. Carcinogenesis

Animal Data. Testosterone has been tested by subcutaneous injection and implantation in mice and rats. The implant induced cervical-uterine tumors in mice, which metastasized in some cases. There is suggestive evidence that injection of testosterone into some strains of female mice increases their susceptibility to hepatoma. Testosterone is also known to increase the number of tumors and decrease the degree of differentiation of chemically induced carcinomas of the liver in rats.

Human Data. There are rare reports of hepatocellular carcinoma in patients receiving long-term therapy with androgens in high doses. Withdrawal of the drugs did not lead to regression of the tumors in all cases.

Geriatric Patients treated with androgens may be at an increased risk for the development of prostatic hypertrophy and prostatic carcinoma.

G. Pregnancy

Teratogenic Effects. Pregnancy Category X (see CONTRAINDICATIONS).

H. Nursing Mothers

It is not known whether androgens are excreted in human milk. Because many drugs are excreted in human milk and because of the potential for serious adverse reactions in nursing infants from androgens, a decision should be made whether to discontinue nursing or to discontinue the drug, taking into account the importance of the drug to the mother.

ADVERSE REACTIONS

Associated with Estrogens

(See Warnings regarding induction of neoplasia, adverse effects on the fetus, increased incidence of gallbladder disease, and adverse effects similar to those of oral contraceptives, including thromboembolism). The following additional adverse reactions have been reported with estrogenic therapy, including oral contraceptives:

1. Genitourinary system.
  Breakthrough bleeding, spotting, change in menstrual flow.
  Dysmenorrhea.
  Premenstrual-like syndrome.
  Amenorrhea during and after treatment.
  Increase in size of uterine fibromyomata.
  Vaginal candidiasis.
  Change in cervical erosion and in degree of cervical secretion.
  Cystitis-like syndrome.
2. Breasts.
  Tenderness, enlargement, secretion.
3. Gastrointestinal.
  Nausea, vomiting.
  Abdominal cramps, bloating.
  Cholestatic jaundice.
4. Skin.
  Chloasma or melasma which may persist when drug is discontinued.
  Erythema multiforme.
  Erythema nodosum.
  Hemorrhagic eruption.
  Loss of scalp hair.
  Hirsutism.
5. Eyes.
  Steepening of corneal curvature.
  Intolerance to contact lenses.
6. CNS.
  Headache, migraine, dizziness.
  Mental depression.
  Chorea.
7. Miscellaneous.
  Increase or decrease in weight.
  Reduced carbohydrate tolerance.
  Aggravation of porphyria.
  Edema.
  Changes in libido.

Associated with Methyltestosterone

A. Endocrine and Urogenital.

1. Female:The most common side effects of androgen therapy are amenorrhea and other menstrual irregularities, inhibition of gonadotropin secretion, and virilization, including deepening of the voice and clitoral enlargement. The latter usually is not reversible after androgens are discontinued. When administered to a pregnant woman androgens cause virilization of external genitalia of the female fetus.

2. Skin and Appendages:Hirsutism, male pattern of baldness, and acne.

3. Fluid and Electrolyte Disturbances:Retention of sodium, chloride, water, potassium, calcium, and inorganic phosphates.

4. Gastrointestinal:Nausea, cholestatic jaundice, alterations in liver function test, rarely hepatocellular neoplasms, and peliosis hepatis (see WARNINGS).

5. Hematologic:Suppression of clotting factors, II, V, VII, and X, bleeding in patients on concomitant anticoagulant therapy, and polycythemia.

6. Nervous System:Increased or decreased libido, headache, anxiety, depression, and generalized paresthesia.

7. Metabolic:Increased serum cholesterol.

8. Miscellaneous:Inflammation and pain at site of intramuscular injection or subcutaneous implantation of testosterone containing pellets, stomatitis with buccal preparations, and rarely anaphylactoid reactions.

OVERDOSAGE

Numerous reports of ingestion of large doses of estrogen-containing oral contraceptives by young children indicate that serious ill effects do not occur. Overdosage of estrogen may cause nausea, and withdrawal bleeding may occur in females.

There have been no reports of acute overdosage with the androgens.

DOSAGE AND ADMINISTRATION

1. Given cyclically for short-term use only:

For treatment of moderate to severe vasomotor symptoms associated with the menopause in patients not improved by estrogen alone.

The lowest dose that will control symptoms should be chosen and medication should be discontinued as promptly as possible.

Administration should be cyclic (e.g., three weeks on and one week off). Attempts to discontinue or taper medication should be made at three to six month intervals.

Usual Dosage Range

1 tablet of ESTERIFIED ESTROGENS AND METHYLTESTOSTERONE FULL STRENGTH or 1 to 2 tablets of ESTERIFIED ESTROGENS AND METHYLTESTOSTERONE HALF STRENGTH daily as recommended by the physician.

Treated patients with an intact uterus should be monitored closely for signs of endometrial cancer and appropriate diagnostic measures should be taken to rule out malignancy in the event of persistent or recurring abnormal vaginal bleeding.

HOW SUPPLIED

ESTERIFIED ESTROGENS AND METHYLTESTOSTERONE TABLETS Full Strength in bottles of 100.

ESTERIFIED ESTROGENS AND METHYLTESTOSTERONE TABLETS Full Strength light pink, capsule-shaped, film-coated, oral tablets, debossed "C020" on obverse and plain on the reverse. Contains: 0.625 mg of Esterified Estrogens, USP and 1.25 mg of Methyltestosterone, USP.

ESTERIFIED ESTROGENS AND METHYLTESTOSTERONE TABLETS Half Strength in bottles of 100.

ESTERIFIED ESTROGENS AND METHYLTESTOSTERONE TABLETS Half Strength light yellow, capsule-shaped, film-coated, oral tablets, debossed "C010" on one side and plain on the reverse. Contains: 1.25 mg of Esterified Estrogens, USP and 2.5 mg of Methyltestosterone, USP.

Store at 20°-25°C (68°-77°F); excursions permitted to 15°-30°C (59°-86°F). [See USP Controlled Room Temperature.]

Rx only

REFERENCES

1. Ziel, H.K. et al.:N. Engl. J. Med. 293:1167-1170, 1975.

2. Smith, D.C., et al.:N. Engl. J. Med. 293:1164-1167, 1975.

3. Mack, T.M., et al.:N. Engl. J. Med. 294:1262-1267, 1976.

4. Weiss, N.S. et al.:N. Engl. J. Med. 294:1259-1262, 1976.

5. Herbst, A.L. et al.:N. Engl. J. Med. 284:878-881, 1971.

6. Greenwald, P., et al.:N. Engl. J. Med. 285:390-392, 1971.

7. Lanier, A., et al.:Mayo Clin. Proc. 48:793-799, 1973.

8. Herbst, A., et al.:Obstet. Gynecol. 40:287-298, 1972.

9. Herbst, A., et al.:Am. J. Obstet. Gynecol. 118:607-615, 1974.

10. Herbst, A., et al.:N. Engl. J. Med. 292:334-339, 1975.

11. Stafl, A., et al.:Obstet. Gynecol. 43:118-128, 1974.

12. Sherman, A.I., et al.:Obstet. Gynecol. 44:531-545, 1974.

13. Gal, I., et al.:Nature 216:83, 1967.

14. Levy, E.P., et al.:Lancet 1:611, 1973.

15. Nora, J., et al.:Lancet 1:941-942, 1973.

16. Janerich, D.T., et al.:N. Engl. J. Med. 291:697-700, 1974.

17. Estrogens for Oral or Parenteral Use: Federal Register 40:8212, 1975.

18. Boston Collaborative Drug Surveillance Program: N. Engl. J. Med. 290:15-19. 1974.

18a. Hoover, R. et al.:N. Engl. J. Med. 295:401-405, 1976.

19. Boston Collaborative Drug Surveillance Program: Lancet 1:1399-1404, 1973.

20. Daniel, D.G., et al.:Lancet 2:287-289, 1967.

21. The Veterans Administration Cooperative Urological Research Group: J. Urol, 98:516-522, 1967.

22. Bailar, J.C.: Lancet 2:560, 1967.

23. Blackard, C., et al.:Cancer 26:249-256, 1970.

24. Royal College of General Practitioners: J.R. Coll, Gen. Pract. 13: 267-279, 1967.

25. Inman, W.H.W., et al.:Br. Med. J. 2:193-199, 1968.

26. Vessey, M.P., et al.:Br. Med. J. 2:651-657, 1969.

27. Sartwell, P.E., et al.:Am. J. Epidemiol, 90:365-380, 1969.

28. Collaborative Group for the Study of Stroke in Young Women: N. Engl. J. Med. 288:871-878, 1973.

29. Collaborative Group for the Study of Stroke in Young Women: J.A.M.A 231:718-722, 1975.

30. Mann, J.I., et al.:Br. Med. J. 2:245-248, 1975.

31. Mann, J.I., et al.:Br. Med. J. 2:241-245, 1975.

32. Inman, W.H.W., et al.:Br. Med. J. 2:203-209, 1970.

33. Stolley, P.D., et al.:Am. J. Epidemiol. 102:197-208, 1975.

34. Vessey, M.P., et al.:Br. Med. J. 3:123-126, 1970.

35. Greene, G.R., et al.:Am. J. Public Health 62:680-685, 1972.

36. Rosenberg, L., et al.:N. Engl. J. Med. 294:1256-1259, 1976.

37. Coronary Drug Project Research Group: J.A.M.A. 214:1303-1313, 1970.

38. Baum, J., et al.:Lancet 2:926-928, 1973.

39. Mays, E.T., et al.:J.A.M.A 235:730-732, 1976.

40. Edmondson, H.A., et al.:N. Engl. J. Med. 294:470-472, 1976.

41. Pfeffer, R.I., et al.:Am. J. Epidemiol. 103:445-456, 1976.

Rx only

Distributed by:
Method Pharmaceuticals, LLC

Southlake. TX 76092

PATIENT INFORMATION

WHAT YOU SHOULD KNOW ABOUT
ESTERIFIED ESTROGENS AND METHYLTESTOSTERONE FULL STRENGTH and ESTERIFIED ESTROGENS AND METHYLTESTOSTERONE HALF STRENGTH

WHAT YOU SHOULD KNOW ABOUT ESTROGENS

Estrogens are female hormones produced by the ovaries. The ovaries make several different kinds of estrogens. In addition, scientists have been able to make a variety of synthetic estrogens. As far as we know, all these estrogens have similar properties and therefore much the same usefulness, side effects, and risks. This leaflet is intended to help you understand what estrogens are used for, the risks involved in their use, and how to use them as safely as possible.

This leaflet includes the most important information about estrogens, but not all the information. If you want to know more, you can ask your doctor or pharmacist to let you read the package insert prepared for the doctor.

USES OF ESTROGEN

Estrogens are prescribed by doctors for a number of purposes, including:

1. To provide estrogen during a period of adjustment when a woman’s ovaries no longer produce it, in order to prevent certain uncomfortable symptoms of estrogen deficiency. (All women normally stop producing estrogens, generally between the ages of 45 and 55; this is called the menopause).
2. To prevent symptoms of estrogen deficiency when a woman’s ovaries have been removed surgically before the natural menopause.
3. To prevent pregnancy: (Estrogens are given along with progestogen, another female hormone; these combinations are called oral contraceptives or birth control pills. Patient labeling is available to women taking oral contraceptives and they will not be discussed in this leaflet.)
4. To treat certain cancers in women and men.

THERE IS NO PROPER USE OF ESTROGENS IN A PREGNANT WOMAN.

ESTROGENS IN THE MENOPAUSE

In the natural course of their lives, all women eventually experience a decrease in estrogen production. This usually occurs between ages 45 and 55 but may occur earlier or later. Sometimes the ovaries may need to be removed before natural menopause by an operation, producing a “surgical menopause.”

When the amount of estrogen in the blood begins to decrease, many women may develop typical symptoms: Feelings of warmth in the face, neck, and chest or sudden intense episodes of heat and sweating throughout the body (called “hot flashes” or “hot flushes”). These symptoms are sometimes very uncomfortable. A few women eventually develop changes in the vagina (called “atrophic vaginitis”) which cause discomfort, especially during and after intercourse.

Estrogens can be prescribed to treat these symptoms of the menopause. It is estimated that considerably more than half of all women undergoing the menopause have only mild symptoms or no symptoms at all and therefore do not need estrogens. Other women may need estrogens for a few months, while their bodies adjust to lower estrogen levels. Sometimes the need will be for periods longer than six months. In an attempt to avoid overstimulation of the uterus (womb), estrogens are usually given cyclically during each month of use, that is three weeks of pills followed by one week without pills.

Sometimes women experience nervous symptoms or depression during menopause. There is no evidence that estrogens are effective for such symptoms and they should not be used to treat them, although other treatment may be needed.

You may have heard that taking estrogens for long periods (years) after the menopause will keep your skin soft and supple and keep you feeling young. There is no evidence that this is so, however, and such long-term treatment carries important risks.

THE DANGERS OF ESTROGENS

1. Cancer of the uterus.If estrogens are used in the postmenopausal period for more than a year, there is an increased risk of endometrial cancer(cancer of the uterus). Women taking estrogens have roughly 5 to 10 times as great a chance of getting this cancer as women who take no estrogens. To put this another way, while a postmenopausal woman not taking estrogens has 1 chance in 1,000 each year of getting cancer of the uterus, a woman taking estrogens has 5 to 10 chances in 1,000 each year. For this reason it is important to take estrogens only when you really need them.

The risk of this cancer is greater the longer estrogens are used and also seems to be greater when larger doses are taken. For this reason, it is important to take the lowest dose of estrogen that will control symptoms and to take it only as long as it is needed.If estrogens are needed for longer periods of time, your doctor will want to reevaluate your need for estrogens at least every six months.

Women using estrogens should report any irregular vaginal bleeding to their doctors; such bleeding may be of no importance, but it can be an early warning of cancer of the uterus. If you have undiagnosed vaginal bleeding, you should not use estrogens until a diagnosis is made and you are certain there is no cancer of the uterus.

2. Other possible cancers. Estrogens can cause development of other tumors in animals, such as tumors of the breast, cervix, vagina, or liver, when given for a long time. At present there is no good evidence that women using estrogen in the menopause have an increased risk of such tumors, but there is no way yet to be sure they do not; and one study raises the possibility that use of estrogens in the menopause may increase the risk of breast cancer many years later. This is a further reason to use estrogens only when clearly needed. While you are taking estrogens, it is important that you go to your doctor at least once a year for a physical examination. Also, if members of your family have had breast cancer or if you have breast nodules or abnormal mammograms (breast x-rays), your doctor may wish to carry out more frequent examinations of your breasts.

3. Gallbladder disease. Women who use estrogens after menopause are more likely to develop gallbladder disease needing surgery as women who do not use estrogens. Birth control pills have a similar effect.
4. Abnormal blood clotting.Oral contraceptives increase the risk of blood clotting in various parts of the body.

This can result in a stroke (if the clot is in the brain), a heart attack (clot in a blood vessel of the heart), or pulmonary embolus (a clot which forms in the legs or pelvis, then breaks off and travels to the lungs). Any of these can be fatal.
At this time use of estrogens in the menopause is not known to cause such blood clotting, but this has not been fully studied and there could still prove to be such a risk. It is recommended that if you have had clotting in the legs or lungs or a heart attack or stroke while you were using estrogens or birth control pills, you should not use estrogens (unless they are being used to treat cancer of the breast or prostate). If you have had a stroke or heart attack or if you have angina pectoris, estrogens should be used with great caution and only if clearly needed (for example, if you have severe symptoms of the menopause).
The larger doses of estrogen used to prevent swelling of the breasts after pregnancy have been reported to cause clotting in the legs and lungs.

SPECIAL WARNING ABOUT PREGNANCY

You should not receive estrogen if you are pregnant. If this should occur, there is a greater than usual chance that the developing child will be born with a birth defect, although the possibility remains fairly small. A female child may have an increased risk of developing cancer of the vagina or cervix later in life (in the teens or twenties). Every possible effort should be made to avoid exposure to estrogens during pregnancy. If exposure occurs, see your doctor.

OTHER EFFECTS OF ESTROGENS

In addition to the serious known risks of estrogens described above, estrogens have the following side effects and potential risks:

1. Nausea and vomiting.The most common side effect of estrogen therapy is nausea. Vomiting is less common.

2. Effects on breasts. Estrogens may cause breast tenderness or enlargement and may cause the breasts to secrete a liquid. These effects are not dangerous.

3. Effects on the uterus.Estrogens may cause benign fibroid tumors of the uterus to get larger.
Some women will have menstrual bleeding when estrogens are stopped. But if the bleeding occurs on days you are still taking estrogens you should report this to your doctor.
4. Effects on liver. Women taking oral contraceptives develop on rare occasions a benign tumor of the liver which can rupture and bleed into the abdomen. So far, these tumors have not been reported in women using estrogens in the menopause, but you should report any swelling or unusual pain or tenderness in the abdomen to your doctor immediately. Women with a past history of jaundice (yellowing of the skin and white parts of the eyes), may get jaundice again during estrogen use. If this occurs, stop taking estrogens and see your doctor.
5. Other effects. Estrogens may cause excess fluid to be retained in the body. This may make some conditions worse, such as epilepsy, migraine, heart disease, or kidney disease.

SUMMARY

Estrogens have important uses, but they have serious risks as well. You must decide, with your doctor, whether the risks are acceptable to you in view of the benefits of the treatment. Except where your doctor had prescribed estrogens for use in special cases of cancer of the breast or prostate, you should not use estrogens if you have cancer of the breast or uterus, are pregnant, have undiagnosed abnormal vaginal bleeding, or have had a stroke, heart attack or angina, or clotting in the legs or lungs in the past while you were taking estrogens.

You can use estrogens as safely as possible by understanding that your doctor will require regular physical examinations while you are taking them and will try to discontinue the drug as soon as possible and use the smallest dose possible. Be alert for signs of trouble including:

1. Abnormal bleeding from the vagina.
2. Pains in the calves or chest or sudden shortness of breath, or coughing blood (indicating possible clots in the legs, heart, or lungs).
3. Severe headache, dizziness, faintness, or changes in vision (indicating possible developing clots in the brain or eye).
4. Breast lumps (you should ask your doctor how to examine your own breasts).
5. Jaundice (yellowing of the skin).
6. Mental depression.

Based on his or her assessment of your medical needs, your doctor has prescribed this drug for you. Do not give the drug to anyone else.

HOW SUPPLIED

ESTERIFIED ESTROGENS AND METHYLTESTOSTERONE TABLETS Half Strength a combination of Esterified Estrogens and Methyltestosterone.

Each capsule-shaped, light pink, film-coated tablet contains: 0.625 mg of Esterified Estrogens, USP and 1.25 mg of Methyltestosterone, USP.

ESTERIFIED ESTROGENS AND METHYLTESTOSTERONE TABLETS Full Strength a combination of Esterified Estrogens and Methyltestosterone.

Each capsule-shaped, light yellow, film-coated tablet contains: 1.25 mg of Esterified Estrogens, USP and 2.5 mg of Methyltestosterone, USP.

All prescription substitutions using this product shall be pursuant to state statutes as applicable.

Store at 20°-25°C (68°-77°F); excursions permitted to 15°-30°C (59°-86°F). [See USP Controlled Room Temperature.]

Rx only

Manufactured By:
Syntho Pharmaceuticals, Inc.
Farmingdale, NY 11735 USA
Distributed By:
Methold Pharmaceuticals, LLC

Southlake, TX 76092

PACKAGE LABEL-PRINCIPAL DISPLAY PANEL

Esterified Estrogen and Methyltestosterone, 0.625 mg/1.25 mg - NDC 58657-407-01 - 100 Tablets Label

Esterified Estrogen and Methyltestosterone , 1.25 mg/2.5 mg - NDC 58657-401-01 - 100 Tablets Label